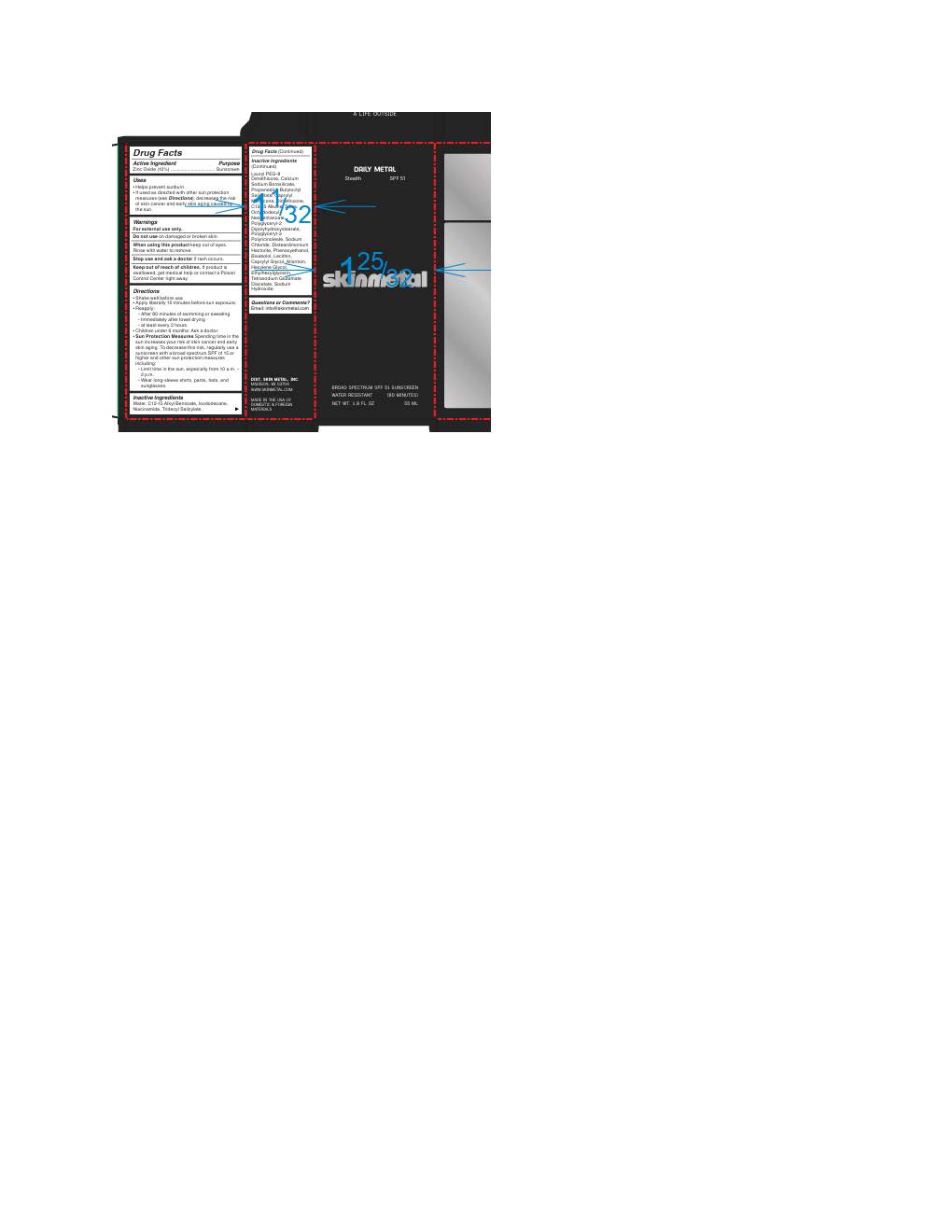 DRUG LABEL: Skin Metal Stealth
NDC: 87098-236 | Form: LOTION
Manufacturer: Skin Metal
Category: otc | Type: HUMAN OTC DRUG LABEL
Date: 20260109

ACTIVE INGREDIENTS: ZINC OXIDE 132 mg/1 mL
INACTIVE INGREDIENTS: SILICON DIOXIDE; POLYGLYCERYL-2 DIPOLYHYDROXYSTEARATE; LECITHIN, SOYBEAN; DIMETHICONE 200; ALKYL (C12-15) BENZOATE; .ALPHA.-BISABOLOL, (+)-; LAURYL PEG-8 DIMETHICONE (300 CPS); BUTYLOCTYL SALICYLATE; OCTYLDODECYL NEOPENTANOATE; ISODODECANE; WATER; NIACINAMIDE; ETHYLHEXYLGLYCERIN; HEXYLENE GLYCOL; PROPANEDIOL; TETRASODIUM GLUTAMATE DIACETATE; SODIUM CHLORIDE; PHENOXYETHANOL; ALLANTOIN; TRIDECYL SALICYLATE; CAPRYLYL METHICONE; SODIUM HYDROXIDE; CALCIUM SODIUM BOROSILICATE; DISTEARDIMONIUM HECTORITE; CAPRYLYL GLYCOL; C13-15 ALKANE

Skin Metal Stealth